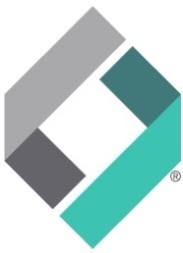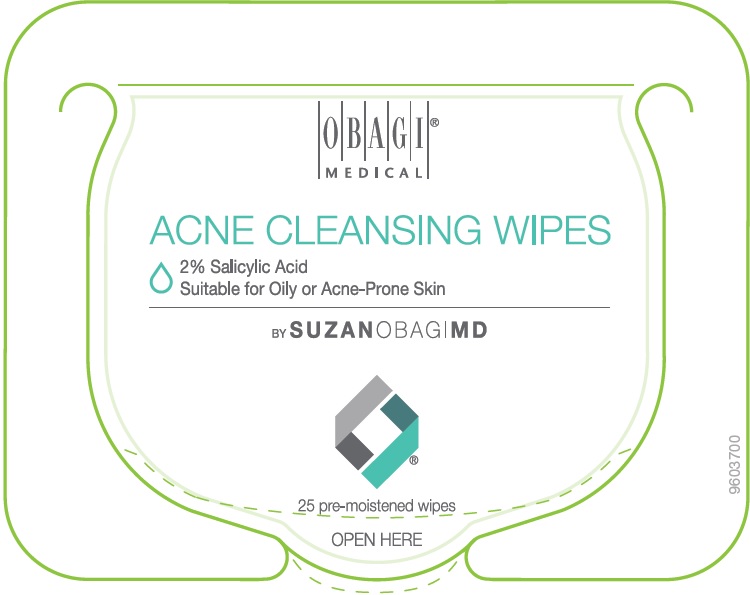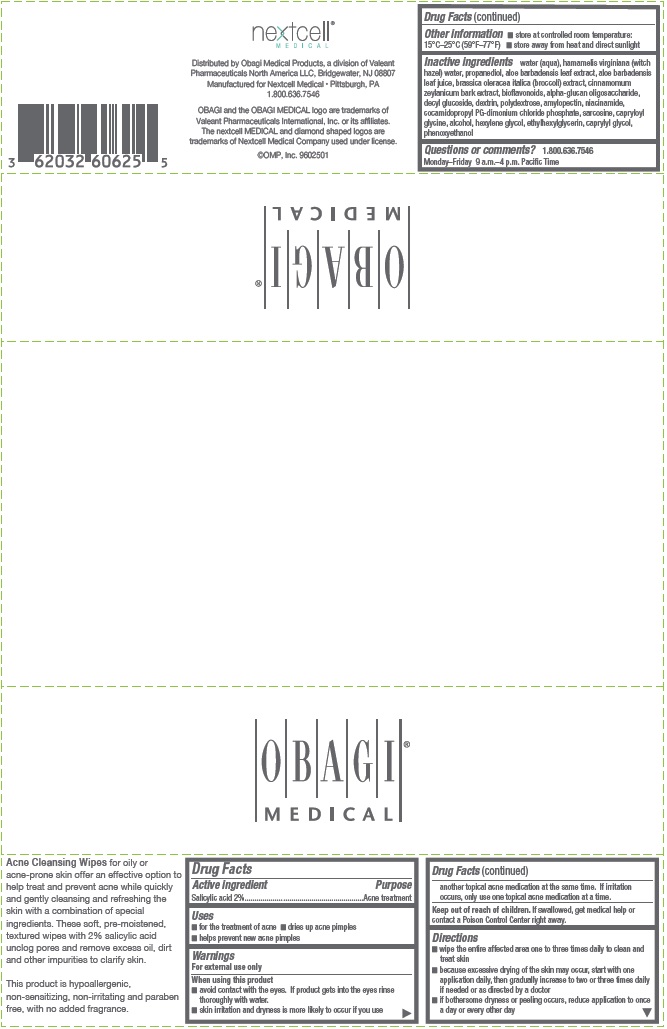 DRUG LABEL: NEXT CELL MEDICAL
NDC: 62032-606 | Form: SWAB
Manufacturer: OMP, Inc.
Category: otc | Type: HUMAN OTC DRUG LABEL
Date: 20180111

ACTIVE INGREDIENTS: SALICYLIC ACID 20 mg/1 1
INACTIVE INGREDIENTS: WATER; HAMAMELIS VIRGINIANA TOP WATER; PROPANEDIOL; ALOE VERA LEAF; BRASSICA OLERACEA VAR. ITALICA WHOLE; CINNAMON; CITRUS BIOFLAVONOIDS; .ALPHA.-GLUCAN OLIGOSACCHARIDE; DECYL GLUCOSIDE; ICODEXTRIN; POLYDEXTROSE; AMYLOPECTIN; NIACINAMIDE; COCAMIDOPROPYL PROPYLENE GLYCOL-DIMONIUM CHLORIDE PHOSPHATE; SARCOSINE; CAPRYLOYL GLYCINE; ALCOHOL; HEXYLENE GLYCOL; ETHYLHEXYLGLYCERIN; CAPRYLYL GLYCOL; PHENOXYETHANOL

OBAGI MEDICAL ACNE CLEANSING WIPES
2% Salicylic Acid
Suitable for Oily or Acne-Prone Skin

Active Ingredient

Salicylic acid 2%

Purpose

Acne treatment

Uses

- for the treatment of acne
- dries up acne pimples
- helps prevent new acne pimples

Warnings

For external use only

When using this product

- avoid contact with the eyes. If product gets into the eyes rinse thoroughly with water.
- skin irritation and dryness is more likely to occur if you use another topical acne medication at the same time. If irritation occurs, only use one topical acne medication at a time.

Keep out of reach of children

- if swallowed, get medical help or contact a Poison Control Center right away.

Directions

- wipe the entire affected area one to three times daily to clean and treat skin
- because excessive drying of the skin may occur, start with one application daily, then gradually increase to two or three times daily if needed or as directed by a doctor
- if bothersome dryness or peeling occurs, reduce application to once a day or every other day

Other information

- store at controlled room temperature: 15°C–25°C (59°F–77°F)
- store away from heat and direct sunlight

Inactive Ingredients

water (aqua), hamamelis virginiana (witch hazel) water, propanediol, aloe barbadensis leaf extract, aloe barbadensis leaf juice, brassica oleracea italica (broccoli) extract, cinnamomum zeylanicum bark extract, bioflavonoids, alpha-glucan oligosaccharide, decyl glucoside, dextrin, polydextrose, amylopectin, niacinamide, cocamidopropyl PG-dimonium chloride phosphate, sarcosine, capryloyl glycine, alcohol, hexylene glycol, ethylhexylglycerin, caprylyl glycol, phenoxyethanol

Questions or comments?

1.800.636.7546

Monday–Friday 9 a.m.–4 p.m. Pacific Time

Principal Display Panel

OBAGI® MEDICAL

ACNE CLEANSING WIPES

2% Salicylic Acid

Suitable for Oily or Acne-Prone Skin

BY SUZAN OBAGI MD

25 pre-moistened wipes

OPEN HERE